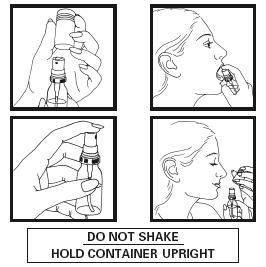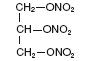 DRUG LABEL: Unknown
Manufacturer: FIRST HORIZON PHARMACEUTICAL CORPORATION
Category: prescription | Type: HUMAN PRESCRIPTION DRUG LABELING
Date: 20060602
DEA Schedule: CIII

Nitrolingual Pumpspray

Nitrolingual® Pumpspray
(nitroglycerin lingual spray)
400 mcg per spray, 60 or 200 Metered Sprays
Before using your Nitrolingual® Pumpspray (nitroglycerin lingual spray) 400 mcg per spray, 60 or 200 metered sprays, read carefully the following directions for use.
Nitrolingual® Pumpspray is a metered dose spray which delivers 48 mg of solution containing 400 mcg of nitroglycerin with each spray. Nitroglycerin is absorbed from the tongue and surrounding mucosa producing a prompt therapeutic effect. It is best to use Nitrolingual® Pumpspray in a sitting position.

INFORMATION FOR THE PATIENT

How to Use Nitrolingual Pumpspray
Before using this product for the first time, the pump must be sprayed 5 times into the air (this is known as priming). The pump should be primed every 6 weeks to remain ready for use. If the product has not been used for 6 weeks, a prime of 1 spray is necessary.

1. Remove the plastic cover.
2. DO NOT SHAKE.
3. Hold the container upright with forefinger on top of the grooved button.
4. Open the mouth and bring the container as close to it as possible.
5. Press the button firmly with the forefinger to release the spray onto or under the tongue. DO NOT INHALE THE SPRAY.
6. Release button and close mouth. Avoid swallowing immediately after administering the spray. The medication should not be expectorated or the mouth rinsed for 5 to 10 minutes following administration.
7. If you require a second administration to obtain relief, repeat steps 4, 5, and 6.
8. Replace the plastic cover.

NOTE: To familiarize yourself with the product and while priming the container, actuate the spray into the air (away from yourself and others). Get the feel of your finger resting on the grooved button so that you can use the spray in the dark. DO NOT SHAKE the container before use. You may wish to keep additional pumpspray containers handy in convenient locations.

Dosage

During an anginal attack, one or two sprays should be administered into your mouth, preferably onto or under the tongue. Do not inhale spray. The medication should not be expectorated or the mouth rinsed for 5 to 10 minutes following administration. A spray may be repeated approximately every 3-5 minutes as needed. No more than three metered sprays are recommended within a 15-minute period. If chest pain persists, prompt medical attention is recommended. Nitrolingual® Pumpspray may be used 5 to 10 minutes prior to engaging in activities which might provoke an acute attack.
There are approximately 60 or 200 metered sprays of nitroglycerin per Nitrolingual® Pumpspray bottle. However, the number of times the medication may be used is dependent on the number of sprays per use (1 or 2 sprays), and frequency of repriming. Each metered spray of Nitrolingual® Pumpspray delivers 400 mcg of nitroglycerin after an initial priming of 5 sprays.The container will remain adequately primed for 6 weeks. If the medication is not used within 6 weeks, it can be adequately reprimed with 1 spray. Longer storage periods without use may require up to 5 repriming sprays.

Precaution

Your physician has determined that this product is likely to help your personal health.
USE THIS PRODUCT AS DIRECTED, BY YOUR PHYSICIAN.
If you have any questions about alternatives, consult with your physician.
Do not share or give your medication to others, particularly those who may appear to be having chest discomfort similar to yours.
Nitrolingual® Pumpspray should be used during an episode of chest pain or may be used 5 to 10 minutes prior to engaging in activities which might provoke an acute attack.
Nitrolingual® Pumpspray is available in a clear glass bottle with a red plastic coating on the exterior. This plastic coating is designed to contain the glass and medication should the bottIe be shattered.
The transparent container can be used for continuous monitoring of the consumption. The end of the pump should be covered by the fluid level. Once fluid falls below the level of the center tube, sprays will not be adequate and the container should be replaced. As with all other sprays, there is a residual volume of fluid at the bottom of the bottle which cannot be used. Nitrolingual®Pumpspray contains 20% alcohol. Do not forcefully open or burn container. Do not spray toward flames. Keep in a safe place and out of the reach of chiIdren.
Store at 25 °C (77 °F); excursions permitted to 15-30 °C (59-86 °F) [see USP Controlled Room Temperature].
Manufactured for FIRST HORIZON PHARMACEUTICAL® CORPORATION,
Alpharetta, GA 30005 by G. Pohl-Boskamp GmbH & Co., D-25551 Hohenlockstedt, Germany.

DESCRIPTION:

Nitroglycerin, an organic nitrate, is a vasodilator which has effects on both arteries and veins. The chemical name for nitroglycerin is 1,2,3-propanetriol trinitrate (C3H5N3O9). The compound has a molecular weight of 227.09. The chemical structure is:
Nitrolingual® Pumpspray (nitroglycerin lingual spray 400 mcg) is a metered dose spray containing nitroglycerin. This product delivers nitroglycerin (400 mcg per spray, 60 or 200 metered sprays) in the form of spray droplets onto or under the tongue. Inactive ingredients: medium-chain triglycerides, dehydrated alcohol, medium-chain partial glycerides, peppermint oil.

CLINICAL PHARMACOLOGY:

The principal pharmacological action of nitroglycerin is relaxation of vascular smooth muscle, producing a vasodilator effect on both peripheral arteries and veins with more prominent effects on the latter. Dilation of the post-capillary vessels, including large veins, promotes peripheral pooling of blood and decreases venous return to the heart, thereby reducing left ventricular end-diastolic pressure (pre-load). Arteriolar relaxation reduces systemic vascular resistance and arterial pressure (after-load).
The mechanism by which nitroglycerin relieves angina pectoris is not fully understood. Myocardial oxygen consumption or demand (as measured by the pressure-rate product, tension-time index, and stroke-work index) is decreased by both the arterial and venous effects of nitroglycerin and presumably, a more favorable supply-demand ratio is achieved.
While the large epicardial coronary arteries are also dilated by nitroglycerin, the extent to which this action contributes to relief of exertional angina is unclear.
Nitroglycerin is rapidly metabolized in vivo, with a liver reductase enzyme having primary importance in the formation of glycerol nitrate metabolites and inorganic nitrate. Two active major metabolites, 1,2- and 1,3-dinitroglycerols, the products of hydrolysis, although less potent as vasodilators, have longer plasma half-lives than the parent compound. The dinitrates are further metabolized to mononitrates (considered biologically inactive with respect to cardiovascular effects) and ultimately glycerol and carbon dioxide.
Therapeutic doses of nitroglycerin may reduce systolic, diastolic and mean arterial blood pressure. Effective coronary perfusion pressure is usually maintained, but can be compromised if blood pressure falls excessively or increased heart rate decreases diastolic filling time.
Elevated central venous and pulmonary capillary wedge pressures, pulmonary vascular resistance and systemic vascular resistance are also reduced by nitroglycerin therapy. Heart rate is usually slightly increased, presumably a reflex response to the fall in blood pressure. Cardiac index may be increased, decreased, or unchanged. Patients with elevated left ventricular filling pressure and systemic vascular resistance values in conjunction with a depressed cardiac index are likely to experience an improvement in cardiac index. On the other hand, when filling pressures and cardiac index are normal, cardiac index may be slightly reduced.
In a pharmacokinetic study when a single 0.8 mg dose of Nitrolingual® Pumpspray was administered to healthy volunteers (n = 24), the mean Cmax and tmax were 1,041pg/mL • min and 7.5 minutes, respectively. Additionally, in these subjects the mean area-under-the-curve (AUC) was 12,769 pg/mL • min.
In a randomized, double-blind single-dose, 5-period cross-over study in 51 patients with exertional angina pectoris significant dose-related increases in exercise tolerance, time to onset of angina and ST-segment depression were seen following doses of 0.2, 0.4, 0.8 and 1.6 mg of nitroglycerin delivered by metered pumpspray as compared to placebo.
Additionally the drug was well tolerated as evidenced by a profile of generally mild to moderate adverse events.

INDICATIONS AND USAGE:

Nitrolingual® Pumpspray is indicated for acute relief of an attack or prophylaxis of angina pectoris due to coronary artery disease.

CONTRAINDICATIONS:

Allergic reactions to organic nitrates are rare. Nitroglycerin is contraindicated in patients who are allergic to it. Nitrolingual® Pumpspray is contraindicated in patients taking certain drugs for erectile dysfunction (phosphodiesterase inhibitors), as their concomitant use can cause severe hypotension. The time course and dose-dependency of this interaction are not known.

WARNINGS:

Amplification of the vasodilatory effects of Nitrolingual® Pumpspray by certain drugs (phosphodiesterase inhibitors) used to treat erectile dysfunction can result in severe hypotension. The time course and dose dependence of this interaction have not been studied. Appropriate supportive care has not been studied, but it seems reasonable to treat this as a nitrate overdose, with elevation of the extremities and with central volume expansion. The use of any form of nitroglycerin during the early days of acute myocardial infarction requires particular attention to hemodynamic monitoring and clinical status.

PRECAUTIONS:

General

Severe hypotension, particularly with upright posture, may occur even with small doses of nitroglycerin. The drug, therefore, should be used with caution in subjects who may have volume depletion from diuretic therapy or in patients who have low systolic blood pressure (e.g., below 90 mm Hg). Paradoxical bradycardia and increased angina pectoris may accompany nitroglycerin-induced hypotension.
Nitrate therapy may aggravate the angina caused by hypertrophic cardiomyopathy.
Tolerance to this drug and cross-tolerance to other nitrates and nitrites may occur. Tolerance to the vascular and anti-anginal effects of nitrates has been demonstrated in clinical trials, experience through occupational exposure, and in isolated tissue experiments in the laboratory.
In industrial workers continuously exposed to nitroglycerin, tolerance clearly occurs. Moreover, physical dependence also occurs since chest pain, acute myocardial infarction, and even sudden death have occurred during temporary withdrawal of nitroglycerin from the workers. In various clinical trials in angina patients, there are reports of anginal attacks being more easily provoked and of rebound in the hemodynamic effects soon after nitrate withdrawal. The relative importance of these observations to the routine, clinical use of nitroglycerin is not known.

PRECAUTIONS: (INFORMATION FOR PATIENTS)

Physicians should discuss with patients that Nitrolingual® Pumpspray should not be used with certain drugs taken for erectile dysfunction (phosphodiesterase inhibitors) because of the risk of lowering their blood pressure dangerously.

DRUG INTERACTIONS:

Alcohol may enhance sensitivity to the hypotensive effects of nitrates. Nitroglycerin acts directly on vascular muscle. Therefore, any other agents that depend on vascular smooth muscle as the final common path can be expected to have decreased or increased effect depending upon the agent.
Marked symptomatic orthostatic hypotension has been reported when calcium channel blockers and oral controlled-release nitroglycerin were used in combination. Dose adjustments of either class of agents may be necessary.
Concomitant use of nitric oxide donors (like Nitrolingual® Pumpspray) and certain drugs for the treatment of erectile dysfunction (phosphodiesterase inhibitors) can amplify their vasodilatory effects, resulting in severe hypotension. The concomitant use of these drugs is contraindicated (see CONTRAINDICATIONS) and alternative therapies should be used to treat acute angina episodes.

CARCINOGENESIS, MUTAGENESIS, IMPAIRMENT OF FERTILITY:

Animal carcinogenesis studies with sublingual nitroglycerin have not been performed.
Rats receiving up to 434 mg/kg/day of dietary nitroglycerin for 2 years developed dose-related fibrotic and neoplastic changes in liver, including carcinomas, and interstitial cell tumors in testes. At high dose, the incidences of hepatocellular carcinomas in both sexes were 52% vs. 0% in controls, and incidences of testicular tumors were 52% vs. 8% in controls. Lifetime dietary administration of up to 1058 mg/kg/day of nitroglycerin was not tumorigenic in mice.
Nitroglycerin was weakly mutagenic in Ames tests performed in two different laboratories. Nevertheless, there was no evidence of mutagenicity in an in vivo dominant lethal assay with male rats treated with doses up to about 363 mg/kg/day, p.o., or in in vitro cytogenic tests in rat and dog tissues.
In a three-generation reproduction study, rats received dietary nitroglycerin at doses up to about 434 mg/kg/day for six months prior to mating of the F0 generation with treatment continuing through successive F1 and F2 generations. The high dose was associated with decreased feed intake and body weight gain in both sexes at all matings. No specific effect on the fertility of the F0 generation was seen. Infertility noted in subsequent generations, however, was attributed to increased interstitial cell tissue and aspermatogenesis in the high-dose males. In this three-generation study there was no clear evidence of teratogenicity.

PREGNANCY:

Pregnancy Category C – Animal teratology studies have not been conducted with nitroglycerin-pumpspray. Teratology studies in rats and rabbits, however, were conducted with topically applied nitroglycerin ointment at doses up to 80 mg/kg/day and 240 mg/kg/day, respectively. No toxic effects on dams or fetuses were seen at any dose tested. There are no adequate and well-controlled studies in pregnant women. Nitroglycerin should be given to pregnant women only if clearly needed.

NURSING MOTHERS:

It is not known whether nitroglycerin is excreted in human milk. Because many drugs are excreted in human milk, caution should be exercised when Nitrolingual® Pumpspray is administered to a nursing woman.

PEDIATRIC USE:

Safety and effectiveness of nitroglycerin in pediatric patients have not been established.

ADVERSE REACTIONS:

Adverse reactions to oral nitroglycerin dosage forms, particularly headache and hypotension, are generally dose-related. In clinical trials at various doses of nitroglycerin, the following adverse effects have been observed:
Headache, which may be severe and persistent, is the most commonly reported side effect of nitroglycerin with an incidence on the order of about 50% in some studies. Cutaneous vasodilation with flushing may occur. Transient episodes of dizziness and weakness, as well as other signs of cerebral ischemia associated with postural hypotension, may occasionally develop. Occasionally, an individual may exhibit marked sensitivity to the hypotensive effects of nitrates and severe responses (nausea, vomiting, weakness, restlessness, pallor, perspiration and collapse) may occur even with therapeutic doses. Drug rash and/or exfoliative dermatitis have been reported in patients receiving nitrate therapy. Nausea and vomiting appear to be uncommon.
Nitrolingual® Pumpspray given to 51 chronic stable angina patients in single doses of 0.4, 0.8 and 1.6 mg as part of a double-blind, 5-period single-dose cross-over study exhibited an adverse event profile that was generally mild to moderate. Adverse events occurring at a frequency greater than 2% included: headache, dizziness, and paresthesia. Less frequently reported events in this trial included (≤2%): dyspnea, pharyngitis, rhinitis, vasodilation, peripheral edema, asthenia, and abdominal pain.

OVERDOSAGE:

Signs and Symptoms:

Nitrate overdosage may result in: severe hypotension, persistent throbbing headache, vertigo, palpitation, visual disturbance, flushing and perspiring skin (later becoming cold and cyanotic), nausea and vomiting (possibly with colic and even bloody diarrhea), syncope (especially in the upright posture), methemoglobinemia with cyanosis and anorexia, initial hyperpnea, dyspnea and slow breathing, slow pulse (dicrotic and intermittent), heart block, increased intracranial pressure with cerebral symptoms of confusion and moderate fever, paralysis and coma followed by clonic convulsions, and possibly death due to circulatory collapse.

Methemoglobinemia:

Case reports of clinically significant methemoglobinemia are rare at conventional doses of organic nitrates. The formation of methemoglobin is dose-related and in the case of genetic abnormalities of hemoglobin that favor methemoglobin formation, even conventional doses of organic nitrates could produce harmful concentrations of methemoglobin.

Treatment of Overdosage:

Keep the patient recumbent in a shock position and comfortably warm. Passive movement of the extremities may aid venous return. Administer oxygen and artificial ventilation, if necessary. If methemoglobinemia is present, administration of methylene blue (1% solution), 1-2 mg per kilogram of body weight intravenously, may be required. If an excessive quantity of Nitrolingual® Pumpspray has been recently swallowed gastric lavage may be of use.

WARNING:

Epinephrine is ineffective in reversing the severe hypotensive events associated with overdosage. It and related compounds are contraindicated in this situation.

DOSAGE AND ADMINISTRATION:

At the onset of an attack, one or two metered sprays should be administered onto or under the tongue. No more than three metered sprays are recommended within a 15-minute period. If the chest pain persists, prompt medical attention is recommended. Nitrolingual® Pumpspray may be used prophylactically five to ten minutes prior to engaging in activities which might precipitate an acute attack.
Each metered spray of Nitrolingual® Pumpspray delivers 48 mg of solution containing 400 mcg of nitroglycerin after an initial priming of 5 sprays. It will remain adequately primed for 6 weeks.If the product is not used within 6 weeks it can be adequately reprimed with 1 spray. Longer storage periods without use may require up to 5 repriming sprays. There are 60 or 200 metered sprays per bottle. The total number of available doses is dependent, however, on the number of sprays per use (1 or 2 sprays), and the frequency of repriming.
The transparent container can be used for continuous monitoring of the consumption. The end of the pump should be covered by the fluid level. Once fluid falls below the level of the center tube, sprays will not be adequate and the container should be replaced. As with all other sprays, there is a residual volume of fluid at the bottom of the bottle which cannot be used.
During application the patient should rest, ideally in the sitting position. The container should be held vertically with the valve head uppermost and the spray orifice as close to the mouth as possible. The dose should preferably be sprayed onto the tongue by pressing the button firmly and the mouth should be closed immediately after each dose. THE SPRAY SHOULD NOT BE INHALED. The medication should not be expectorated or the mouth rinsed for 5 to 10 minutes following administration. Patients should be instructed to familiarize themselves with the position of the spray orifice, which can be identified by the finger rest on top of the valve, in order to facilitate orientation for administration at night.

HOW SUPPLIED:

Each box of Nitrolingual® Pumpspray, contains one clear glass bottle coated with red transparent plastic which assists in containing the glass and medication should the bottle be shattered. Each unit contains 4.9 g (NDC 59630- 300-65) or 12 g (NDC 59630-300-20) (Net Content) of nitroglycerin lingual spray which will deliver 60 or 200 metered sprays containing 400 mcgs of nitroglycerin per spray after priming.
Store at 25 °C (77 °F); excursions permitted to 15-30 °C (59-86 °F) [see USP Controlled Room Temperature].
Note: Nitrolingual® Pumpspray contains 20% alcohol. Do not forcefully open or burn container after use. Do not spray toward flames.
Rx Only.
Manufactured for FIRST HORIZON PHARMACEUTICAL® CORPORATION,
Alpharetta, GA 30005 by G. Pohl-Boskamp GmbH & Co., D-25551
Hohenlockstedt, Germany.
NLPS-PI-2
Rev. 10/05